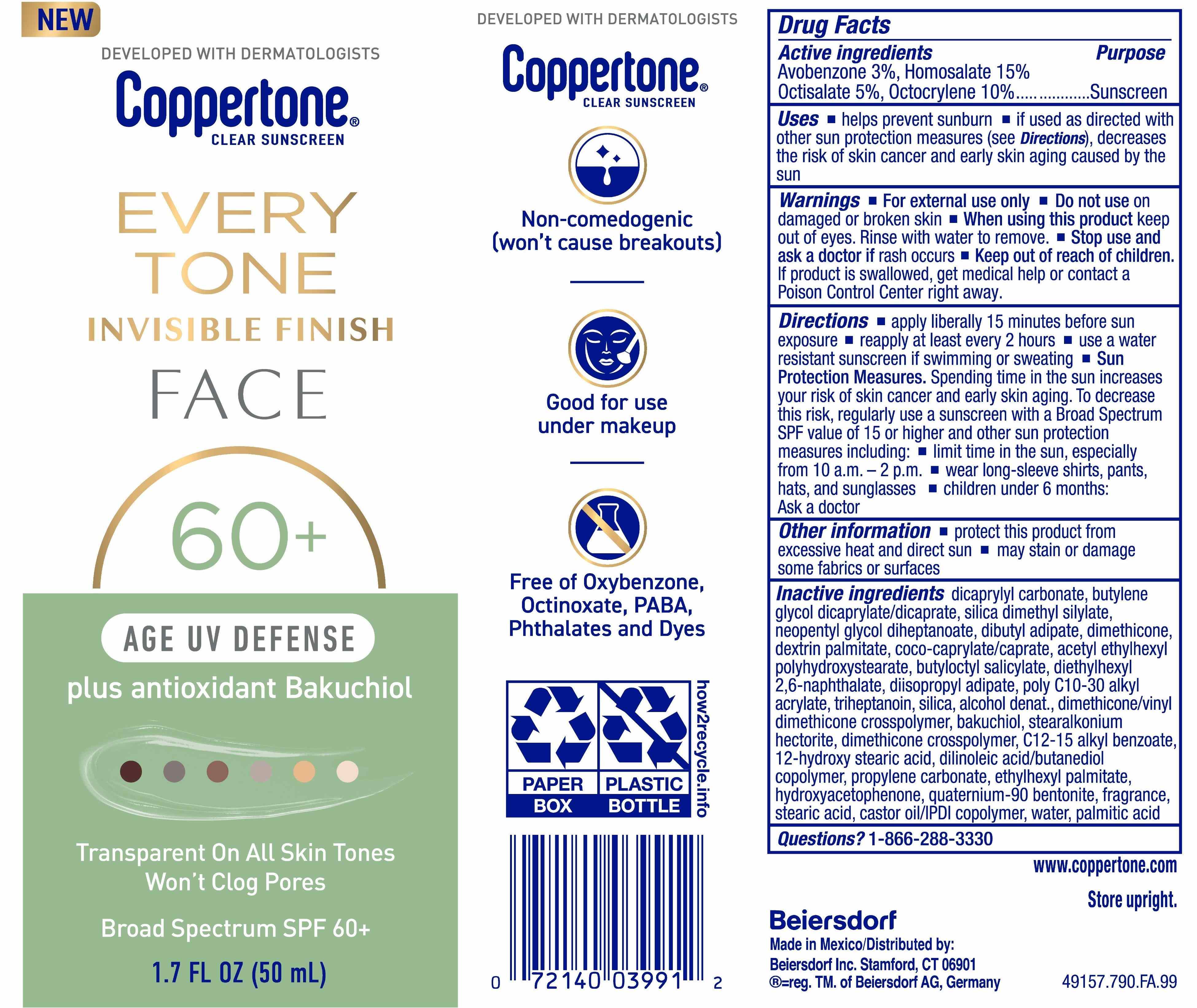 DRUG LABEL: Coppertone Every Tone Age Defense Sunscreen SPF 60
NDC: 66800-8002 | Form: LOTION
Manufacturer: Beiersdorf Inc
Category: otc | Type: HUMAN OTC DRUG LABEL
Date: 20251231

ACTIVE INGREDIENTS: HOMOSALATE 15 g/100 g; OCTISALATE 5 g/100 g; OCTOCRYLENE 10 g/100 g; AVOBENZONE 3 g/100 g
INACTIVE INGREDIENTS: DEXTRIN PALMITATE (CORN; 20000 MW); ALCOHOL; STEARALKONIUM HECTORITE; C12-20 ALKYL BENZOATE; WATER; QUATERNIUM-90 BENTONITE; ETHYLHEXYL PALMITATE; SILICA DIMETHYL SILYLATE; PROPYLENE CARBONATE; HYDROXYACETOPHENONE; DIISOPROPYL ADIPATE; FRAGRANCE FRESH CITRUS FLORAL ORC1501495; STEARIC ACID; PALMITIC ACID; COCO-CAPRYLATE/CAPRATE; DIMETHICONE, UNSPECIFIED; DICAPRYLYL CARBONATE; DILINOLEIC ACID/BUTANEDIOL COPOLYMER; 12-HYDROXYSTEARIC ACID; BUTYLENE GLYCOL DICAPRYLATE/DICAPRATE; DIBUTYL ADIPATE; TRIHEPTANOIN; CASTOR OIL/IPDI COPOLYMER; BUTYLOCTYL SALICYLATE; CALCIUM SILICATE; ACRYLATES/C10-30 ALKYL ACRYLATE CROSSPOLYMER (60000 MPA.S); DIMETHICONE/VINYL DIMETHICONE CROSSPOLYMER (HARD PARTICLE); BAKUCHIOL; DIETHYLHEXYL 2,6-NAPHTHALATE; NEOPENTYL GLYCOL DIHEPTANOATE; DIMETHICONE CROSSPOLYMER; POLYVINYL ACETATE

Coppertone Every Tone Face Age Defense Clear Sunscreen SPF 60+

Active ingredients

Avobenzone 3%, Homosalate 15%,
Octisalate 5%, Octocrylene 10%

Purpose

Sunscreen

Uses

■ helps prevent sunburn
■ if used as directed with other sun protection measures (see Directions),
decreases the risk of skin cancer and early skin aging caused by the sun

Warnings

For external use only

Do not useon damaged or broken skin

WHEN USING

When using this productkeep out of eyes. Rinse with water to remove.

Stop use and ask a doctor ifrash occurs

Keep out of reach of children.If product is swallowed, get medical help or
contact a Poison Control Center right away.

Directions

■ apply liberally 15 minutes before sun exposure
■ reapply at least every 2 hours
■ use a water resistant sunscreen if swimming or sweating
■ Sun Protection Measures.Spending time in the sun increases your risk of skin
cancer and early skin aging. To decrease this risk, regularly use a sunscreen
with a Broad Spectrum SPF value of 15 or higher and other sun protection
measures including:
■ limit time in the sun, especially from 10 a.m. – 2 p.m.
■ wear long-sleeve shirts, pants, hats, and sunglasses
■ children under 6 months: Ask a doctor

Other information

■ protect this product from excessive heat and direct sun
■ may stain or damage some fabrics or surfaces

Inactive ingredients

dicaprylyl carbonate, butylene glycol dicaprylate/dicaprate, silica dimethyl silylate, neopentyl glycol diheptanoate, dibutyl adipate, dimethicone, dextrin palmitate, coco- caprylate/caprate, acetyl ethylhexyl polyhydroxystearate, butyloctyl salicylate, diethylhexyl 2,6-naphthalate, diisopropyl adipate, poly C10-30 alkyl acrylate, triheptanoin, silica, alcohol denat., dimethicone/vinyl dimethicone crosspolymer, bakuchiol, stearalkonium hectorite, dimethicone crosspolymer, C12-15 alkyl benzoate, 12-hydroxy stearic acid, dilinoleic acid/butanediol copolymer, propylene carbonate, ethylhexyl palmitate, hydroxyacetophenone, quaternium-90 bentonite, fragrance, stearic acid, castor oil/IPDI copolymer, water, palmitic acid

Questions?

1-866-288-3330

PACKAGE LABEL

NEW

Coppertone® Clear Sunscreen

Every Tone Invisible Finish

Face 60+

Age UV Defense plus Bakuchiol

Transparent on all skin tones

Won't clog pores

Broad Spectrum SPF 60+

1.7 FL OZ (50 mL)